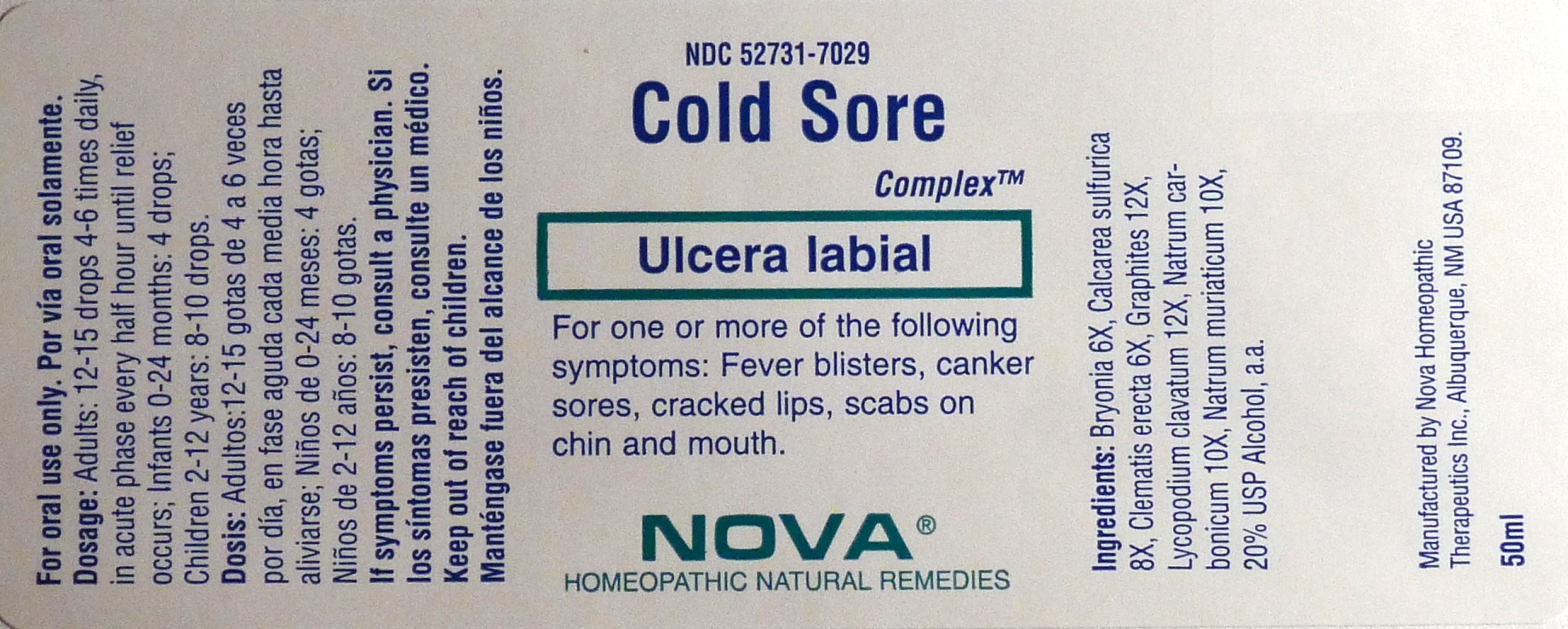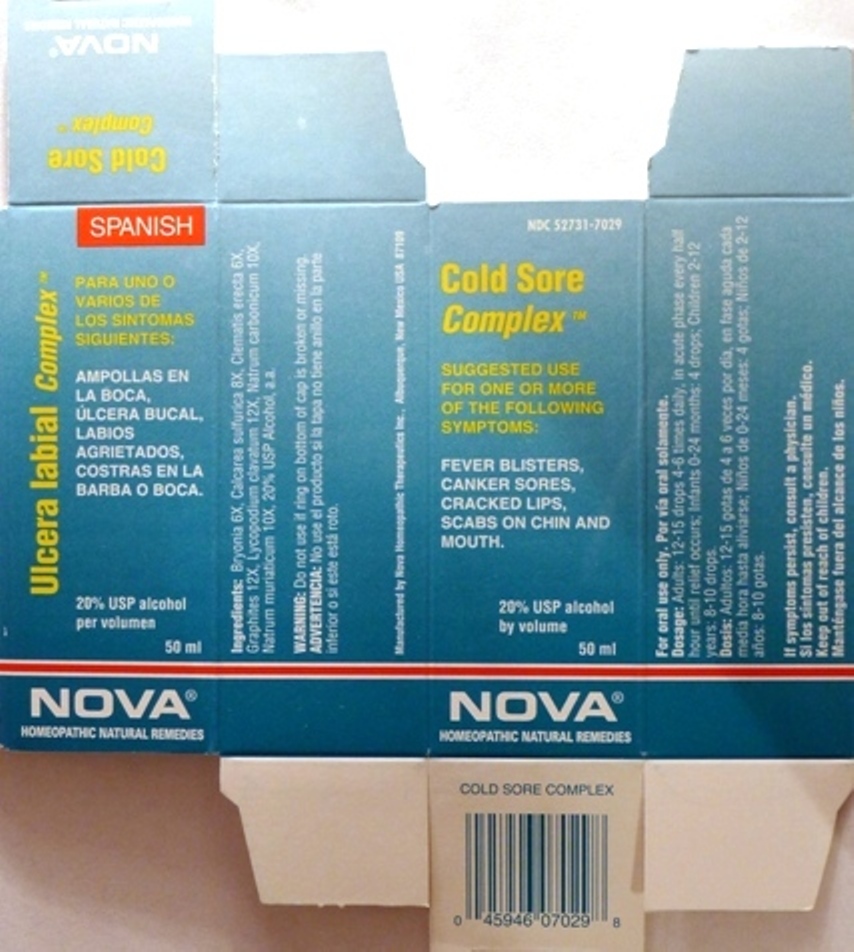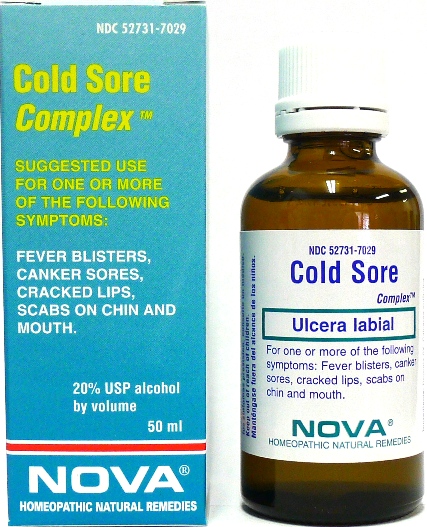 DRUG LABEL: Cold Sore Complex
NDC: 52731-7029 | Form: LIQUID
Manufacturer: Nova Homeopathic Therapeutics, Inc.
Category: homeopathic | Type: HUMAN OTC DRUG LABEL
Date: 20110601

ACTIVE INGREDIENTS: BRYONIA ALBA ROOT 6 [hp_X]/1 mL; CALCIUM SULFATE ANHYDROUS 8 [hp_X]/1 mL; CLEMATIS RECTA FLOWERING TOP 6 [hp_X]/1 mL; GRAPHITE 12 [hp_X]/1 mL; LYCOPODIUM CLAVATUM SPORE 12 [hp_X]/1 mL; SODIUM CARBONATE 10 [hp_X]/1 mL; SODIUM CHLORIDE 10 [hp_X]/1 mL
INACTIVE INGREDIENTS: ALCOHOL

Cold Sore Complex

Purpose:

Suggested use for one or more of the following symptoms:

Fever blisters, canker sores, cracked lips, scabs on chin and mouth.

Usage and Dosage:

For oral use only.

DOSAGE AND ADMINISTRATION

Adults:
In Acute Phase:
12-15 drops until relief occurs
When Relief Occurs:
12-15 drops, 4-6 times per day
Children 2-12 years:
8-10 drops, 4-6 times per day
Infants 0-24 months:
4 drops, 4-6 times per day

Warnings:

Keep out of reach of children.

WARNINGS

If symptoms persist, consult a physician.
Do not use if ring on bottom of cap is broken or missing.

Active Ingredients:

Bryonia 6X, Calcarea sulfurica 8X, Clematis erecta 6X, Graphites 12X, Lycopodium clavatum 12X, Natrum carbonicum 10X, Natrum muriaticum 10X

Inactive Ingredients:

Alcohol, 20% USP

QUESTIONS

Manufactured by Nova Homeopathic Therapeutics Inc., Albuquerque, New Mexico USA 87109
1-800-225-8094

PACKAGE LABEL

Cold Sore Complex Product

Cold Sore Complex Bottle Label

Cold Sore Complex Box